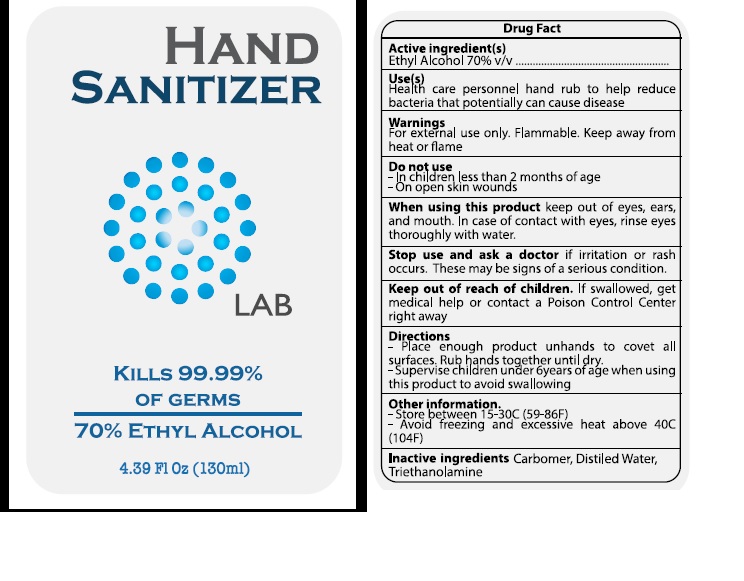 DRUG LABEL: Supernova Lab
NDC: 76726-001 | Form: SOLUTION
Manufacturer: Supernova Coating, S.A. de C.V.
Category: otc | Type: HUMAN OTC DRUG LABEL
Date: 20200425

ACTIVE INGREDIENTS: ALCOHOL 70 mL/100 mL
INACTIVE INGREDIENTS: CARBOMER 940; WATER; TROLAMINE

Supernova Lab

Active Ingredient

Ethyl Alcohol

Purpose

Antibacterial

Uses

Health care personnel hand rub to help reduce bacteria that potentially can cause diseases.

Warnings

For external use only.

Flammable. Keep away from heat or flame

Do not use- In children less than 2 months of age
- On open skin wounds.

When using this product keep out of eyes, ears, and mouth. In case of contact with eyes, rinse eyes thoroughly with water

Directions

- Place enough product onhands to cover all surfaces. Rub hands together until dry.

- Supervise children under 6 years of age when using this product to avoid swallowing.

Other information

- Store between 15-30C (59-86F)

- Avoid freezing and excessive heat above 40C(104F)

Keep out of reach of children

If swallowed, get medical help or contact a poison control center right away.

Inactive Ingredient

Triethanolamine,Distilled Water,Carbomer